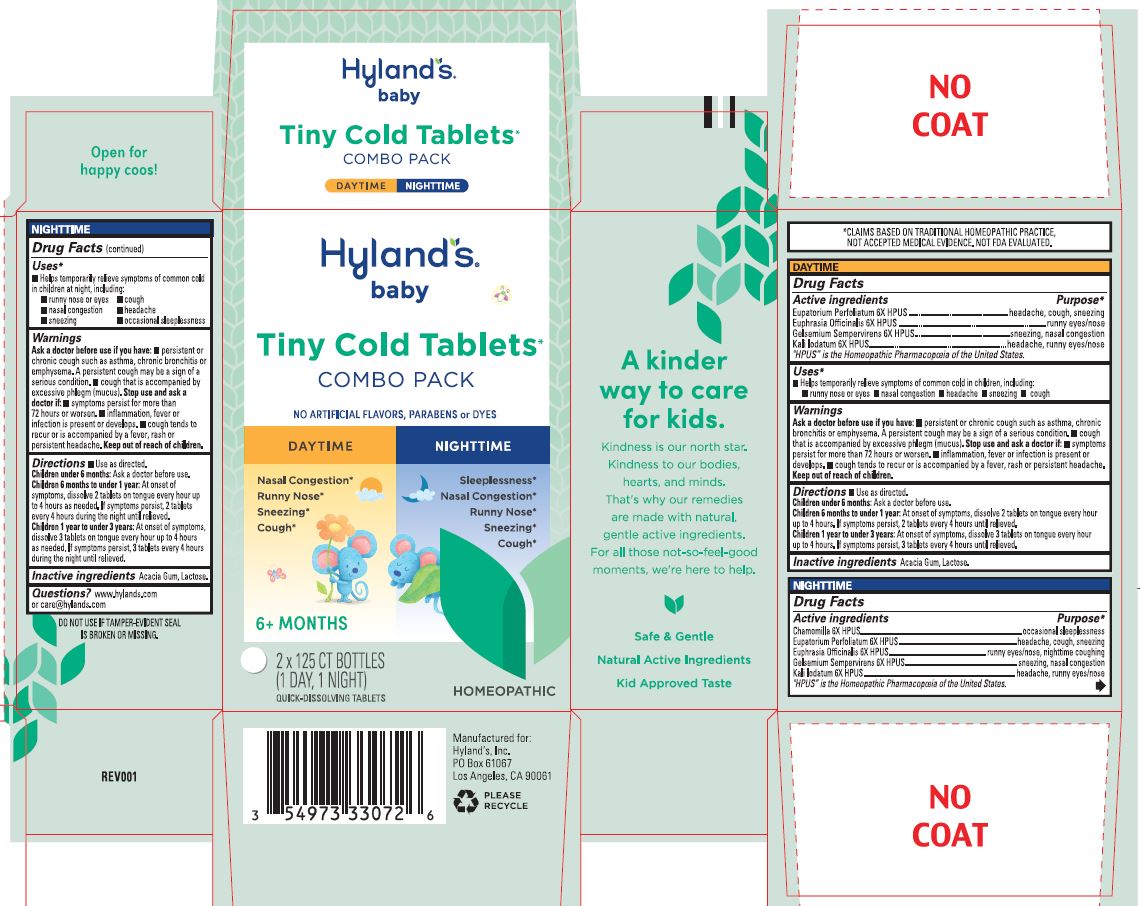 DRUG LABEL: Baby Tiny Cold Daytime and Nighttime
NDC: 54973-3307 | Form: KIT | Route: ORAL
Manufacturer: Hyland's Inc.
Category: homeopathic | Type: HUMAN OTC DRUG LABEL
Date: 20250402

ACTIVE INGREDIENTS: EUPATORIUM PERFOLIATUM FLOWERING TOP 6 [hp_X]/1 1; EUPHRASIA STRICTA 6 [hp_X]/1 1; GELSEMIUM SEMPERVIRENS ROOT 6 [hp_X]/1 1; POTASSIUM IODIDE 6 [hp_X]/1 1; MATRICARIA RECUTITA 6 [hp_X]/1 1; EUPATORIUM PERFOLIATUM FLOWERING TOP 6 [hp_X]/1 1; EUPHRASIA STRICTA 6 [hp_X]/1 1; GELSEMIUM SEMPERVIRENS ROOT 6 [hp_X]/1 1; POTASSIUM IODIDE 6 [hp_X]/1 1
INACTIVE INGREDIENTS: ACACIA; LACTOSE, UNSPECIFIED FORM; ACACIA; LACTOSE, UNSPECIFIED FORM

Baby Tiny Cold Tablets Combo Pack

Indications and Usage

Daytime Uses

 Temporarily relieves symptoms of common cold in children, including:

 runny nose or eyes  nasal congestion  headache  sneezing  cough

Nighttime Uses

■ Temporarily relieves symptoms of common cold in children at night, including: ■ runny nose or eyes ■ cough ■ nasal congestion ■ headache ■ sneezing ■ occasional sleeplessness

■ Use as directed.

Children under 6 months: Ask a doctor before use.

Children 6 months to under 1 year: At onset of symptoms, dissolve 2 tablets on tongue
every hour up to 4 hours. If symptoms persist, 2 tablets every 4 hours until relieved.
Children 1 year to under 3 years: At onset of symptoms, dissolve 3 tablets on tongue
every hour up to 4 hours. If symptoms persist, 3 tablets every 4 hours until relieved.

Active ingredients | Purpose
Eupatorium Perfoliatum 6X HPUS | headache, cough, sneezing
Euphrasia Officinalis 6X HPUS | runny eyes/nose
Gelsemium Sempervirens 6X HPUS | sneezing, nasal congestion
Kali Iodatum 6X HPUS | headache, runny eyes/nose

"HPUS” is the Homeopathic Pharmacopoeia of the United States.

Uses

■ Helps temporarily relieve symptoms of common cold in children, including: ■ runny nose or eyes ■ nasal congestion ■ headache ■ sneezing ■ cough

Ask a doctor before use if you have

■ persistent or chronic cough such as asthma, chronic bronchitis or emphysema. A persistent cough may be a sign of a serious condition. ■ cough that is accompanied by excessive phlegm (mucus).

Stop use and ask a doctor if

■ symptoms persist for more than 72 hours or worsen. ■ inflammation, fever or infection is present or develops. ■ cough tends to recur or is accompanied by a fever, rash or persistent headache.

Directions

■ Use as directed.

Children under 6 months: | Ask a doctor before use.
Children 6 months to under 1 year: | At onset of symptoms, dissolve 2 tablets on tongue every hour up to 4 hours. If symptoms persist, 2 tablets every 4 hours until relieved.
Children 1 year to under 3 years: | At onset of symptoms, dissolve 3 tablets on tongue every hour up to 4 hours. If symptoms persist, 3 tablets every 4 hours until relieved.

Inactive ingredients

Acacia Gum, Lactose.

Active ingredients | Purpose
Chamomilla 6X HPUS | occasional sleeplessness
Eupatorium Perfoliatum 6X HPUS | headache, cough, sneezing
Euphrasia Officinalis 6X HPUS | runny eyes/nose, nighttime coughing
Gelsemium Sempervirens 6X HPUS | sneezing, nasal congestion
Kali Iodatum 6X HPUS | headache, runny eyes/nose

"HPUS” is the Homeopathic Pharmacopoeia of the United States.

Uses

■ Helps temporarily relieve symptoms of common cold in children at night, including:
■ runny nose or eyes ■ cough ■ nasal congestion
■ headache ■ sneezing ■ occasional sleeplessness

Ask a doctor before use if you have

■ persistent or chronic cough such as asthma, chronic bronchitis or emphysema. A persistent cough may be a sign of a serious condition. ■ cough that is accompanied by excessive phlegm (mucus).

Stop use and ask a doctor if

■ symptoms persist for more than 72 hours or worsen. ■ inflammation, fever or infection is present or develops. ■ cough tends to
recur or is accompanied by a fever, rash or persistent headache.

Directions

■ Use as directed

Children under 6 months: | Ask a doctor before use.
Children 6 months to under 1 year: | At onset of symptoms, dissolve 2 tablets on tongue every hour up to 4 hours as needed. If symptoms persist, 2 tablets every 4 hours during the night until relieved.
Children 1 year to under 3 years: | At onset of symptoms, dissolve 3 tablets on tongue every hour up to 4 hours as needed. If symptoms persist, 3 tablets every 4 hours during the night until relieved.

Inactive ingredients

Acacia Gum, Lactose.

Questions?

www.hylands.com or care@hylands.com

Indications and Usage

DAYTIME

Uses

■ Helps temporarily relieve symptoms of common cold in children, including:
■ runny nose or eyes ■ nasal congestion ■ headache ■ sneezing ■ cough

NIGHTTIME

Uses

■ Helps temporarily relieve symptoms of common cold in children at night, including:
■ runny nose or eyes ■ cough ■ nasal congestion
■ headache ■ sneezing ■ occasional sleeplessness

PURPOSE

Helps temporarily relieve symptoms of common cold in children at night, including: runny nose or eyes, cough, nasal congestion,
headache, sneezing, occasional sleeplessness.

Principal Display Panel

Hyland's

•baby•

Tiny Cold Tablets*

COMBO PACK

NO ARTIFICIAL FLAVORS, PARABENS or DYES

DAYTIME

Nasal Congestion

Runny Nose

Sneezing

Cough

NIGHTTIME

Sleeplessness

Nasal Congestion

Runny Nose

Sneezing

Cough

6+ MONTHS

2 x 125 CT BOTTLES

(1 DAY, 1 NIGHT)

QUICK-DISSOLVING TABLETS

HOMEOPATHIC